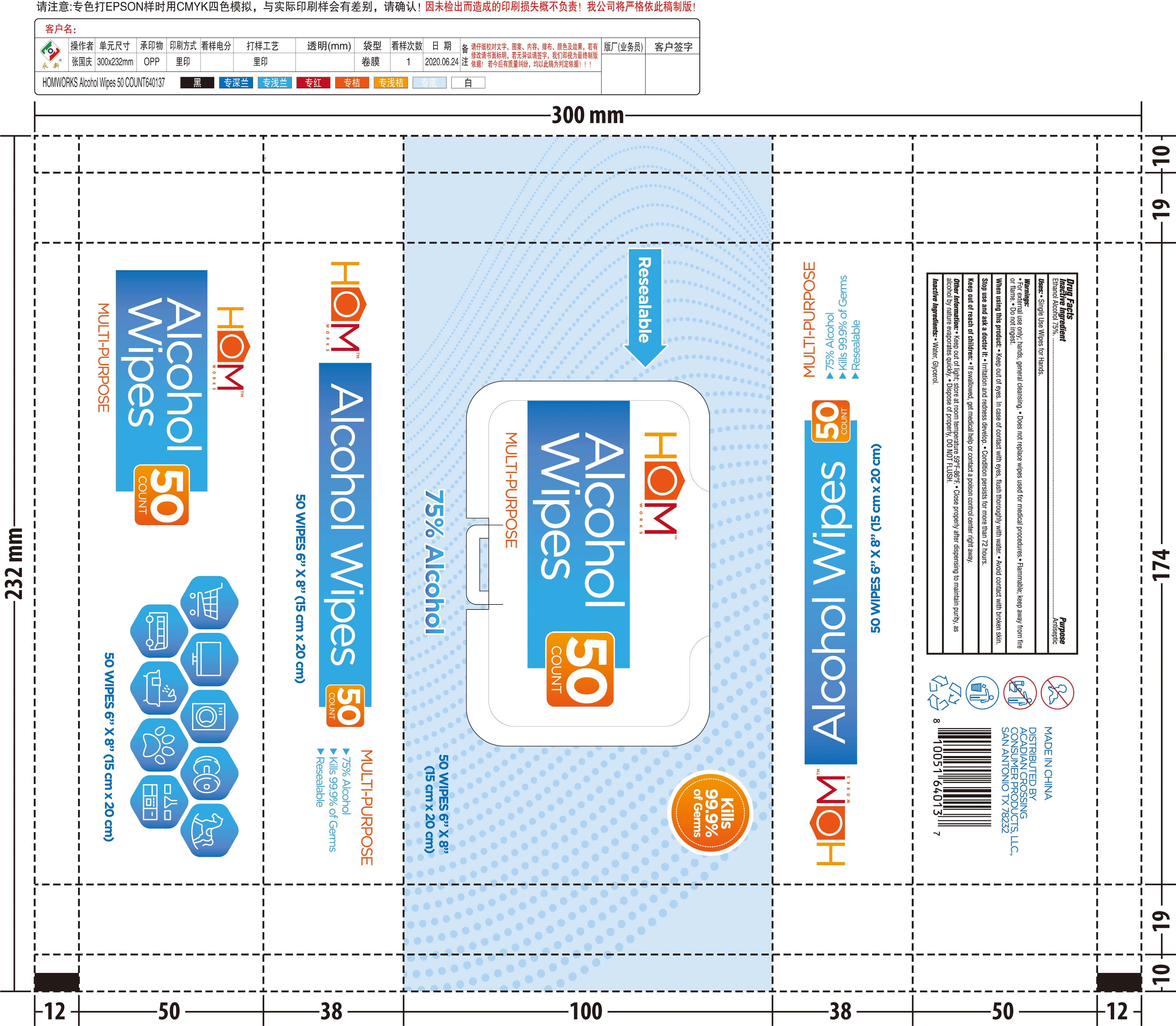 DRUG LABEL: sanitizing wipes
NDC: 79589-001 | Form: CLOTH
Manufacturer: Arch Point Group LLC
Category: otc | Type: HUMAN OTC DRUG LABEL
Date: 20200709

ACTIVE INGREDIENTS: ALCOHOL 0.75 mL/1 g
INACTIVE INGREDIENTS: WATER; GLYCERIN

sanitizing wipes

ACTIVE INGREDIENT

Alcohol 75%. Purpose: Antiseptic

PURPOSE

Antiseptic

Use(s)

Single Use Wipes for Hands

Warning

- For external use only; hands, general cleansing.
- Does not replace wipes used for medical procedures.
- Flammable; Keep away from fire or flame
- Do not ingest

When using this product

- Keep our of eyes. In case of contact with eyes, flush thoroughly with water.
- Avoid contact with broken skin.

Do not use

on open skin wounds

Stop use and ask a doctor if

- Irritation and redness develop
- condition persists for more than 72 hours

KEEP OUT OF REACH OF CHILDREN

Keep our of reach of children. If swallowed, get medical help or contact a poison control center right away.

Directions

Close properly after dispensing to maintain purity, as alcohol by nature evaporates quickly.
Dispose of properly, DO NOT FLUSH

Other information

- Keep out of light; store at room temperature 59F-86F.
- Close properly after dispensing to maintain purity, as alcohol by nature evaporates quickly.
- Dispose of properly, DO NOT FLUSH.

Inactive Ingredients

Water, Glycerol

Package Label - Principal Display Panel

50 PCS NDC: 79589-001-01